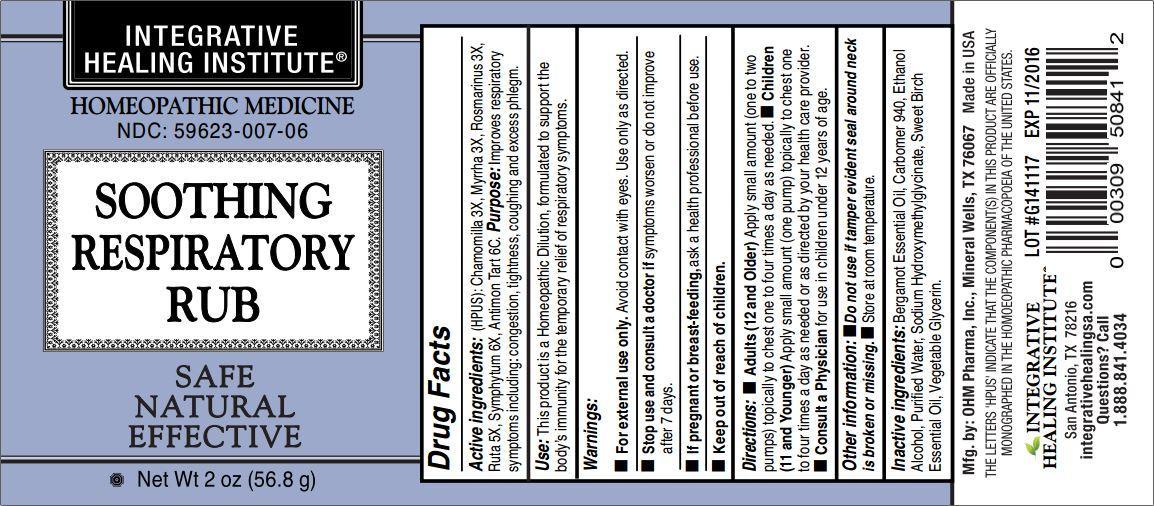 DRUG LABEL: Soothing Respiratory Rub

NDC: 59623-007 | Form: GEL
Manufacturer: Integrative Healing Institute, LLC
Category: homeopathic | Type: HUMAN OTC DRUG LABEL
Date: 20211229

ACTIVE INGREDIENTS: MATRICARIA RECUTITA 3 [hp_X]/1 g; MYRRH 3 [hp_X]/1 g; ROSMARINUS OFFICINALIS FLOWERING TOP 3 [hp_X]/1 g; RUTA GRAVEOLENS FLOWERING TOP 5 [hp_X]/1 g; COMFREY ROOT 6 [hp_X]/1 g; ANTIMONY POTASSIUM TARTRATE 6 [hp_C]/1 g
INACTIVE INGREDIENTS: BERGAMOT OIL; CARBOMER HOMOPOLYMER TYPE C (ALLYL PENTAERYTHRITOL CROSSLINKED); ALCOHOL; WATER; SODIUM HYDROXYMETHYLGLYCINATE; METHYL SALICYLATE; GLYCERIN

SOOTHING RESPIRATORY RUB

ACTIVE INGREDIENT

Active ingredients (HPUS): Chamomilla 3X, Myrrha 3X, Rosmarinus 3X, Ruta 5X, Symphytum 6X, Antimon Tart 6C.

PURPOSE

Purpose: Improves respiratory symptoms including: congestion, tightness, coughing and excess phlegm.

INDICATIONS AND USAGE

Use: This product is a Homeopathic Dilution, formulated to support the body's immunity for the temporary relief of respiratory symptoms.

Warnings:

- For external use only. Avoid contact with eyes. Use only as directed.
- Stop use and consult a doctor if symptoms worsen or do not improve after 7 days.
- If pregnant or breast-feeding, ask a health professional before use.

- Keep out of reach of children.

Directions:

- Adults (12 and Older) Apply small amount (one to two pumps) topically to chest one to four times a day as needed.
- Children (11 and Younger) Apply small amount (one pump) topically to chest one to four times a day as needed or as directed by your health care provider.
- Consult a Physician for use in children under 12 years of age.

Other information:

- Do not use if tamper evident seal around neck is broken or missing.
- Store at room temperature.

INACTIVE INGREDIENT

Inactive ingredients: Bergamot Essential Oil, Carbomer 940, Ethanol Alcohol, Purified Water, Sodium Hydroxymethylglycinate, Sweet Birch Essential Oil, Vegetable Glycerin.

OTHER SAFETY INFORMATION

Mfg. by: OHM Pharma, Inc., Mineral Wells, TX 76067

Made in USA

THE LETTERS 'HPUS' INDICATE THAT THE COMPONENT(S) IN THIS PRODUCT ARE OFFICIALLY MONOGRAPHED IN THE HOMOEOPATHIC PHARMACOPOEIA OF THE UNITED STATES.

QUESTIONS

INTEGRATIVE HEALING INSTITUTE®

San Antonio, TX 78216

integrativehealingsa.com

Questions? Call 1.888.841.4034

PACKAGE LABEL

INTEGRATIVE HEALING INSTITUTE®

HOMEOPATHIC MEDICINE

NDC: 59623-007-06

SOOTHING RESPIRATORY RUB

SAFE

NATURAL

EFFECTIVE

Net Wt 2 oz (56.8 g)